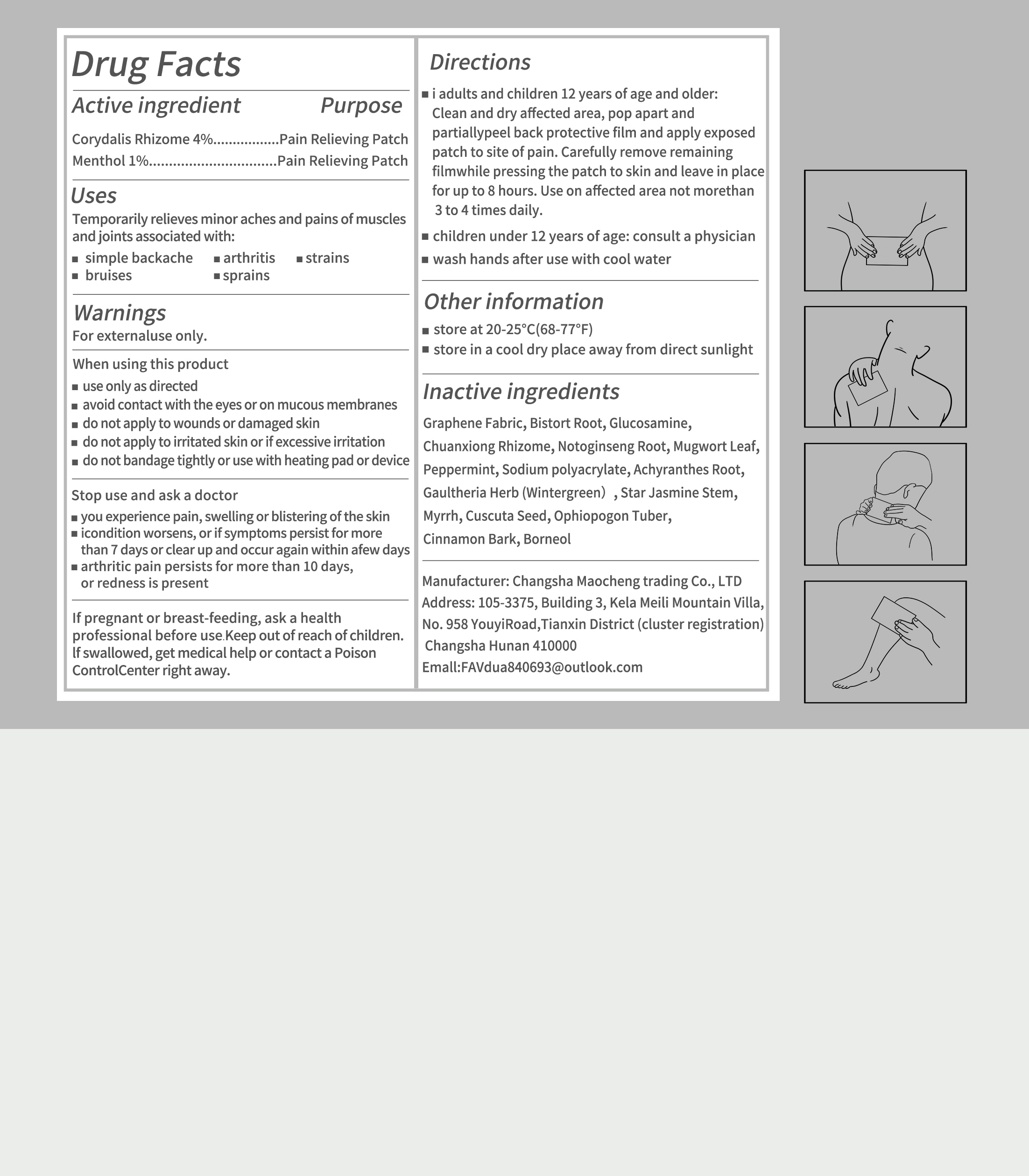 DRUG LABEL: Graphene Far Infrared Herbal Pain Relief Patches
NDC: 84876-006 | Form: PATCH
Manufacturer: Changsha Maocheng Trading Co., Ltd
Category: otc | Type: HUMAN OTC DRUG LABEL
Date: 20250802

ACTIVE INGREDIENTS: CORYDALIS YANHUSUO TUBER 4 g/100 g; MENTHOL 1 g/100 g
INACTIVE INGREDIENTS: PANAX NOTOGINSENG ROOT; GRAPHITE; OPHIOPOGON JAPONICUS ROOT; BISTORTA OFFICINALIS ROOT; MYRRH OIL; BORNEOL; PEPPERMINT; GAULTHERIA PROCUMBENS (WINTERGREEN) LEAF OIL; ARTEMISIA VULGARIS OIL; TRACHELOSPERMUM JASMINOIDES STEM; GLUCOSAMINE; LIGUSTICUM SINENSE SUBSP. CHUANXIONG ROOT; ACHYRANTHES BIDENTATA ROOT; SODIUM POLYACRYLATE (2500000 MW); CUSCUTA JAPONICA SEED; CINNAMON

ACTIVE INGREDIENT

Corydalis Rhizome 4%
Menthol 1%

INACTIVE INGREDIENT

Graphene Fabric
Bistort Root
Glucosamine
Chuanxiong Rhizome
Notoginseng Root
Mugwort Leaf
Peppermint
Sodium polyacrylate
Achyranthes Root
Gaultheria Herb (Wintergreen)
Star Jasmine Stem
Myrrh
Cuscuta Seed
Ophiopogon Tuber
Cinnamon Bark
Borneol

PURPOSE

Temporarily relieves minor aches and pains of muscles

WARNINGS

For externaluse only.

WHEN USING

use only as directedavoid contact with the eyes or on mucous membranesdo not apply to wounds or damaged skindo not apply to irritated skin or ifexcessive irritationdo not bandage tightly or use with heating pad or device

Keep out of reach of children. lfswallowed, get medical help or contact a Poison Control
Center right away.

INDICATIONS AND USAGE

adults and children 12 years of age and older: Clean and dry affected area, pop apartand partiallypeel back protective film and apply exposed patch to site of pain, Carefullyremove remaining filmwhile pressing the patch to skin and leave in place for up to 8hours. Use on affected area not morethan 3 to 4 times daily.children under 12 years of age: consult a physicianwash hands after use with cool water

DOSAGE AND ADMINISTRATION

Carefullyremove remaining filmwhile pressing the patch to skin and leave in place for up to 8hours. Use on affected area not morethan 3 to 4 times daily.

OTHER SAFETY INFORMATION

store at 20-25°C(68-77°F)store in a cool dry place away from direct sunlight